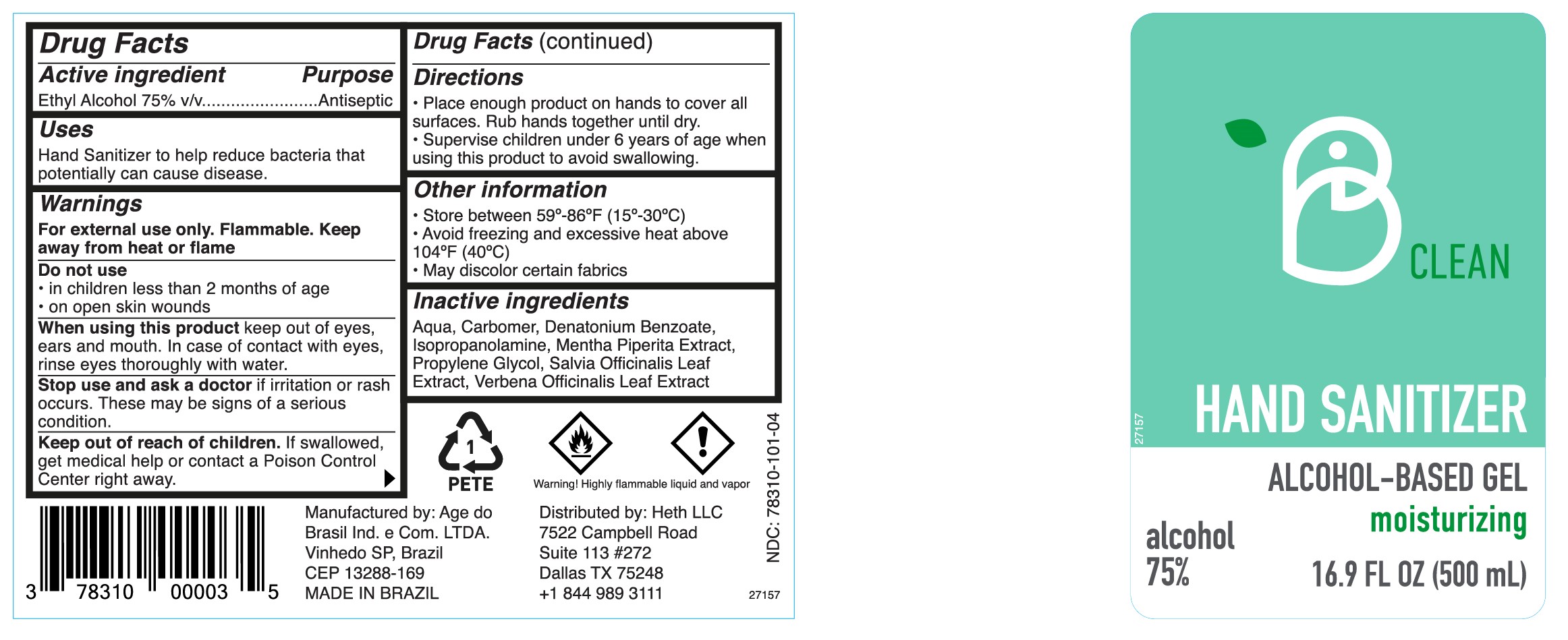 DRUG LABEL: B CLEAN HAND SANITIZER
NDC: 78310-300 | Form: GEL
Manufacturer: HETH LLC
Category: otc | Type: HUMAN OTC DRUG LABEL
Date: 20210101

ACTIVE INGREDIENTS: ALCOHOL 60 kg/100 kg
INACTIVE INGREDIENTS: PROPYLENE GLYCOL; MENTHA PIPERITA; ISOPROPANOLAMINE; VERBENA OFFICINALIS LEAF; DENATONIUM BENZOATE; METHACRYLIC ACID - ETHYL ACRYLATE COPOLYMER (1:1) TYPE A; SAGE; WATER

B Clean - Hand Sanitizer (AQUA)

Active Ingredient

Ethyl Alcohol 75% v/v. Purpose: Antiseptic

Purpose

Antiseptic, Hand Sanitizer

Use

Hand Sanitizer to help reduce bacteria that potentially can cause disease.

Warnings

For external use only. Flammable. Keep away from heat or flame

Do not use

- in children less than 2 months of age
- on open skin wounds

When using this product keep out of eyes, ears and mouth. In case of contact with eyes, rinse eyes thoroughly with water.

Stop use and ask a doctor if irritation or rash occurs. These may be signs of a serious condition.

Keep out of reach of children. if swallowed, get medical help or contact a Poison Control Center right away.

Directions

- Place enough product on hands to cover all surfaces. Rub hands together until dry.
- Supervise children under 6 years of age when using this product to avoid swallowing.

Other information

- Store between 59º-86ºF (15º-30ºC)
- Avoid freezing and excessive heat above 104ºF (40ºC)
- May discolor certain fabrics

Inactive Ingredients

Aqua, Carbomer, Denatonium Benzoate, Isopropanolamine, Mentha Piperita Extract, Propylene Glycol, Salvia Officinalis Leaf Extract, Verbena Officinalis Leaf Extract

Package Label - Principal Display Panel

B CLEAN

HAND SANITIZER
ALCOHOL-BASED GEL
moisturizing

alcohol 75%

Distributed by: Heth LLC
7522 Campbell Road
Suite 113 #272
Dallas TX 75248
+1 844 989 3111

MADE IN BRAZIL